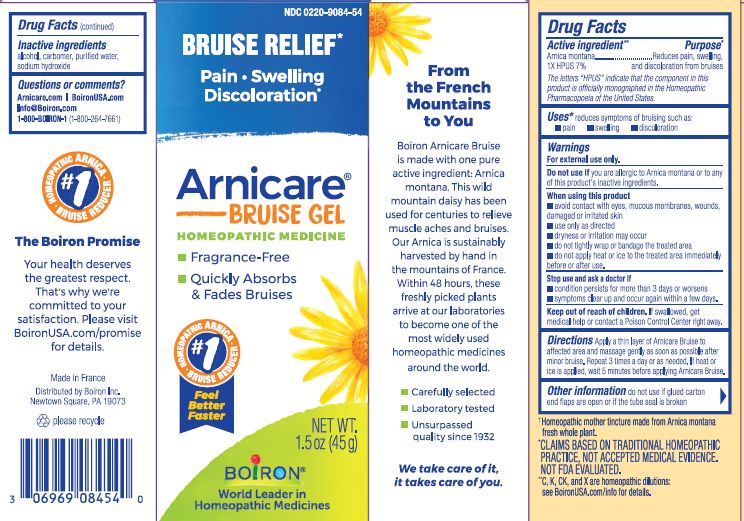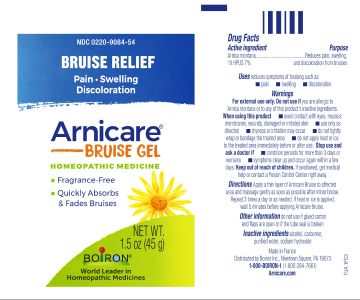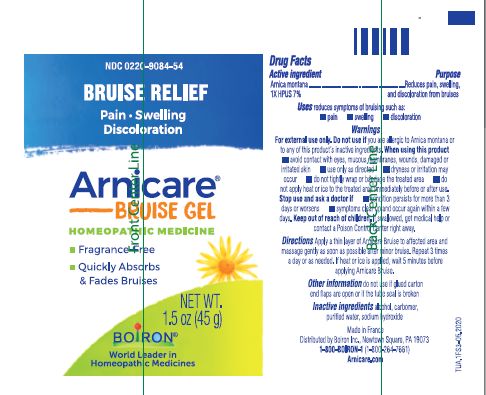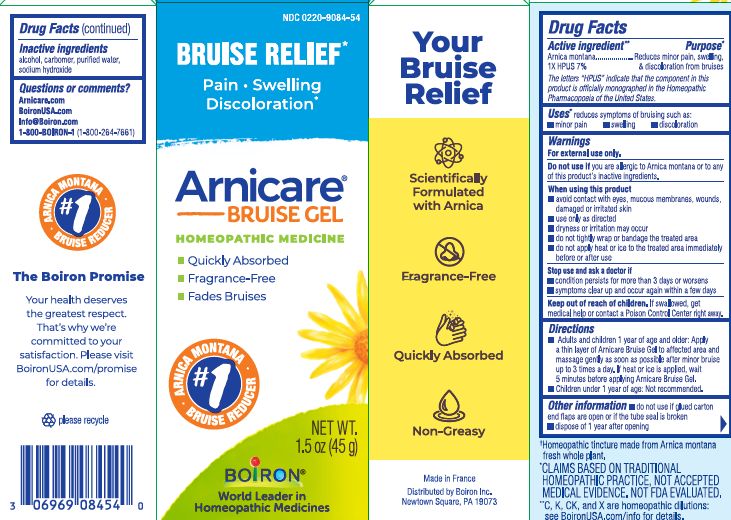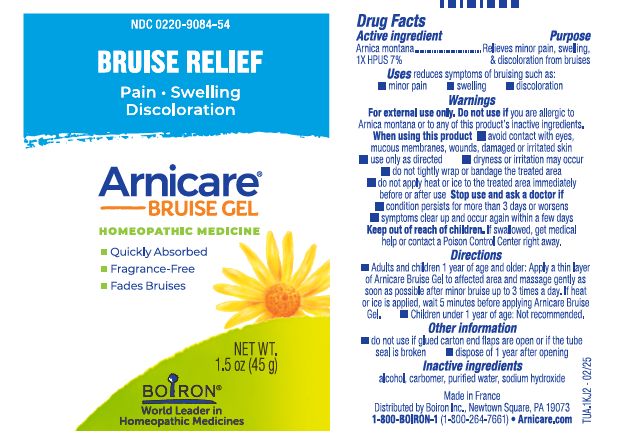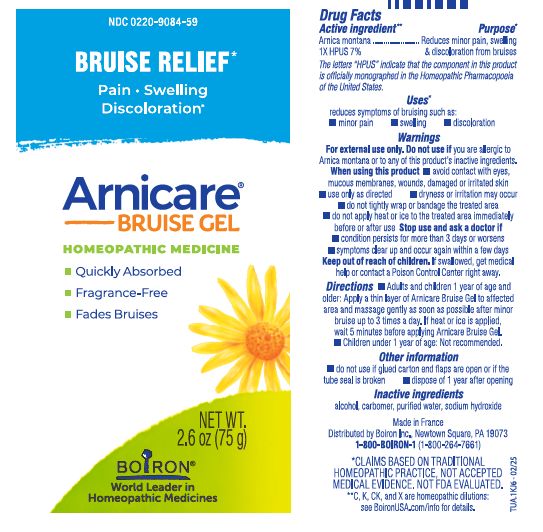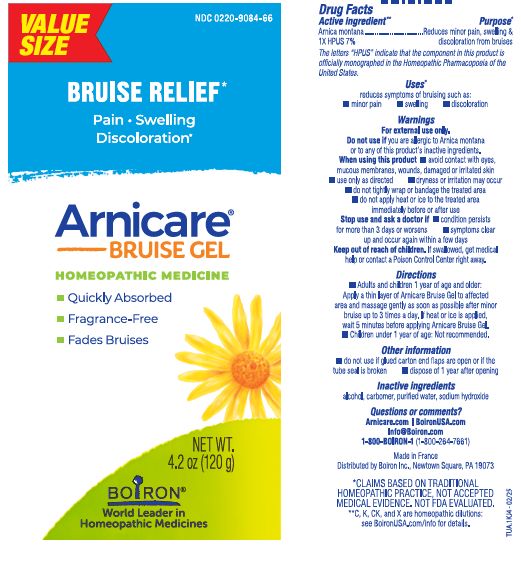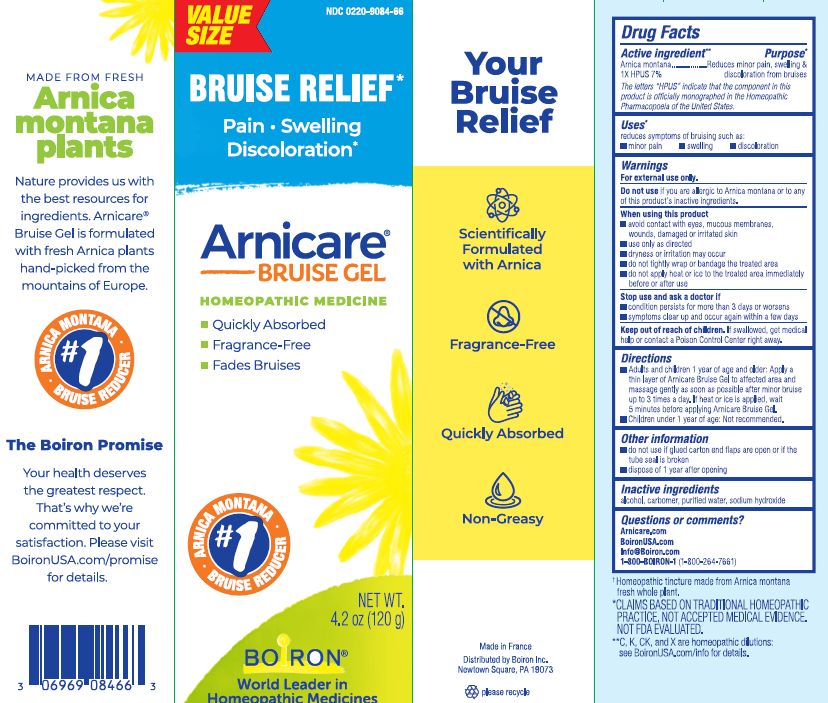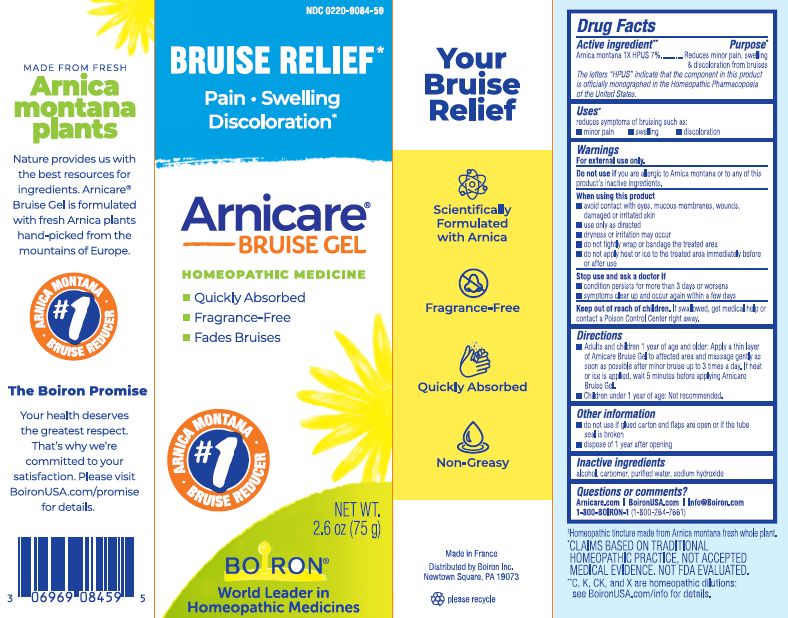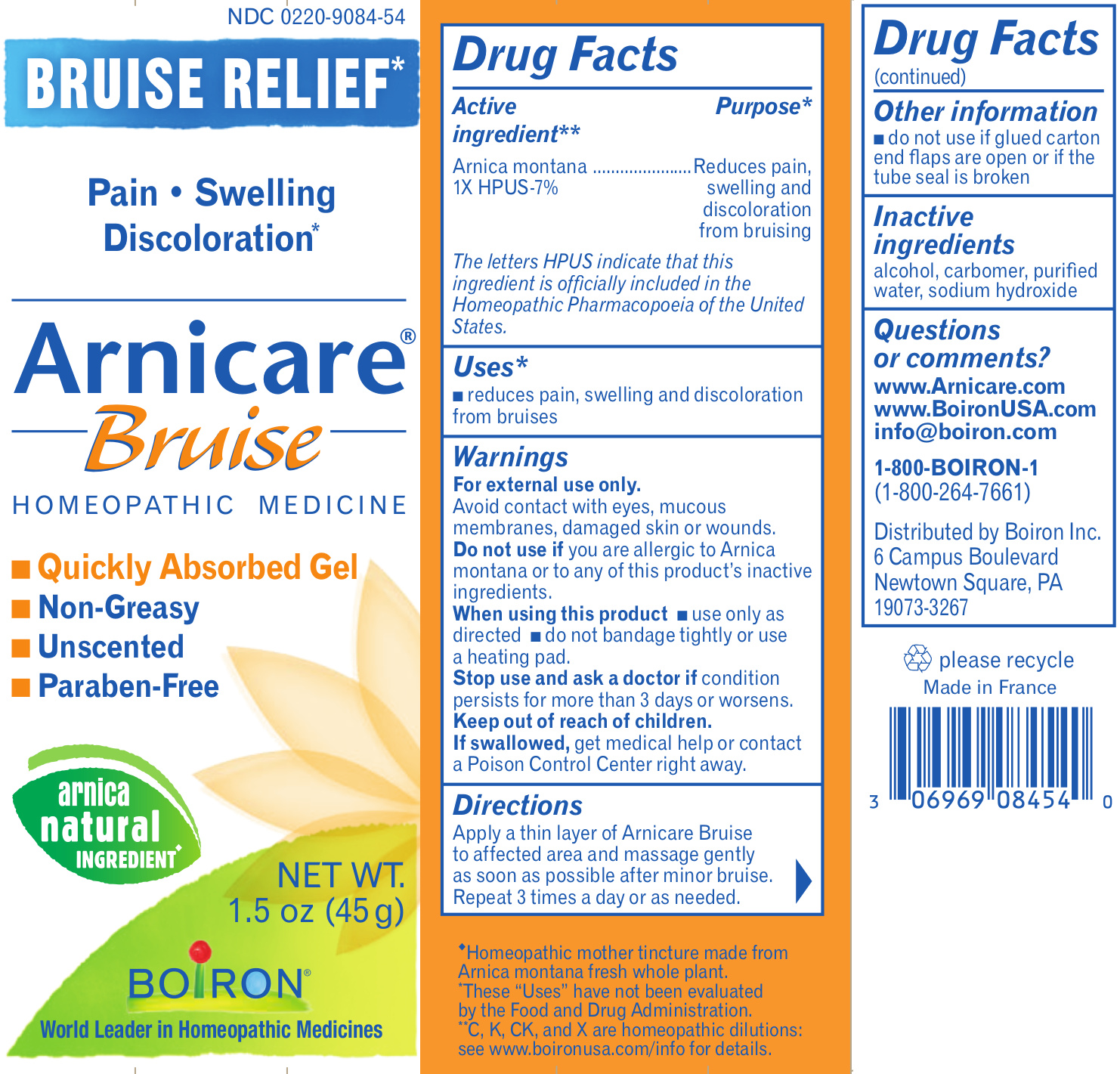 DRUG LABEL: Arnicare Bruise
NDC: 0220-9084 | Form: GEL
Manufacturer: Laboratoires Boiron
Category: homeopathic | Type: HUMAN OTC DRUG LABEL
Date: 20250314

ACTIVE INGREDIENTS: ARNICA MONTANA 1 [hp_X]/1 g
INACTIVE INGREDIENTS: WATER; SODIUM HYDROXIDE; ALCOHOL; CARBOMER HOMOPOLYMER TYPE C

Arnicare Bruise

Active Ingredients**

Arnica montana 1X HPUS 7%

The letters "HPUS" indicate that the components in this product are officially monographed in the Homeopathic Pharmacopoeia of the United States.

Purpose*

Arnica montana 1X HPUS - Reduces minor pain, swelling & discoloration from bruises

Uses*

reduces symptoms of bruising such as:

- minor pain
- swelling
- discoloration

Warnings

For external use only.

Do not use if you are allergic to Arnica montana or to any of this product’s inactive ingredients.

When using this product

- avoid contact with eyes, mucus membranes, wounds, damaged or irritated skin
- use only as directed
- dryness or irritation may occur
- do not tightly wrap or bandage the treated area
- do not apply heat or ice to the treated area immediately before or after use

Stop use and ask a doctor if

- condition persists for more than 3 days or worsens
- symptoms clear up and occur again within a few days

Keep out of reach of children. If swallowed, get medical help or contact a Poison Control Center right away.

Directions

- Adults and children 1 year of age and older: Apply a thin layer of Arnicare Bruise Gel to affected area and massage gently as soon as possible after minor bruise up to 3 times a day. If heat or ice is applied, wait 5 minutes before applying Arnicare Bruise Gel.
- Children under 1 year of age: Not recommended.

Other information

- do not use if glued carton end flaps are open or if the tube seal is broken
- dispose of 1 year after opening

Inactive ingredients

alcohol, carbomer, purified water, sodium hydroxide

Questions, Comments?

Arnicare.com
BoironUSA.com
info@boiron.com
1-800-BOIRON-1
(1-800-264-7661)
Distributed by Boiron Inc.
Newtown Square, PA 19073-3267

1.5 oz (45 g)

2.6 oz (75 g)

4.2 oz (120 g)

Fragrance-Free

Quickly Absorbed

Fades Bruises

ɨ Homeopathic mother tincture made from Arnica montana fresh whole plant.

*CLAIMS BASED ON TRADITIONAL HOMEOPATHIC PRACTICE NOT ACCEPTED MEDICAL EVIDENCE. NOT FDA EVALUATED.
*C,K,CK, and X are homeopathic dilutions: see BoironUSA.com/info for details.